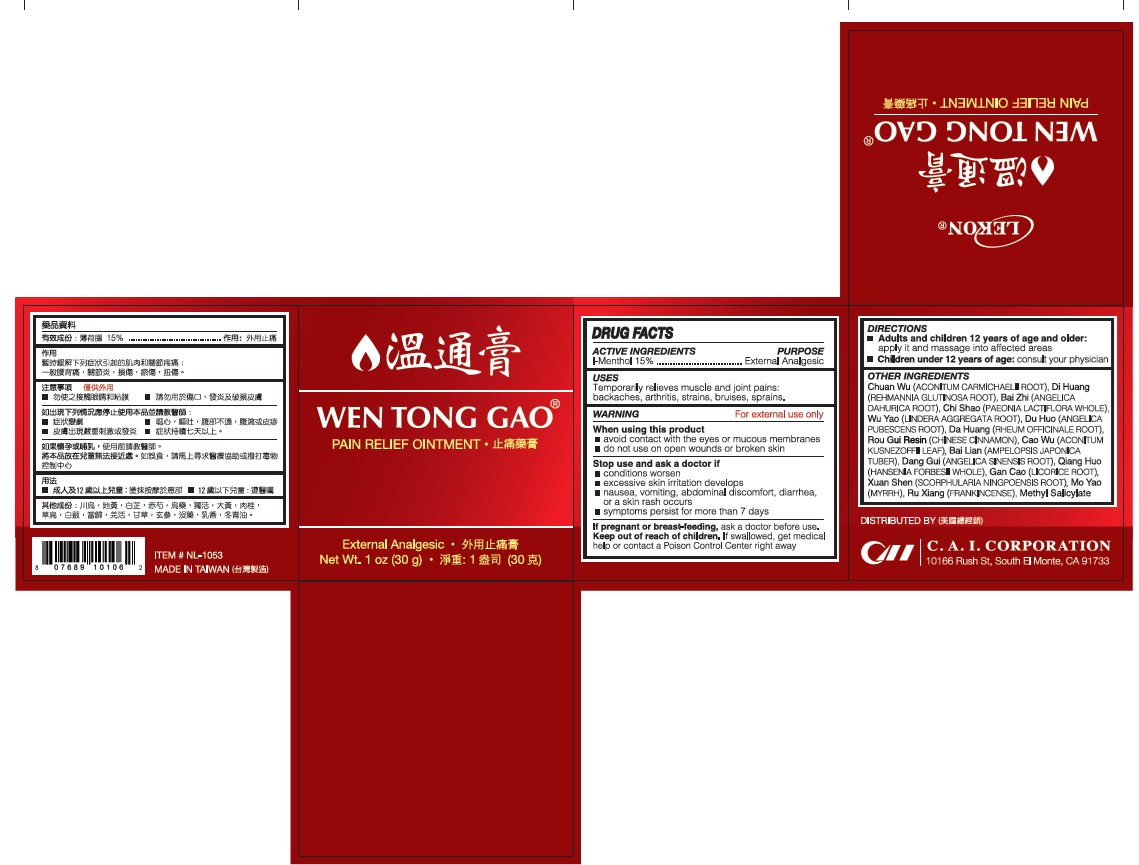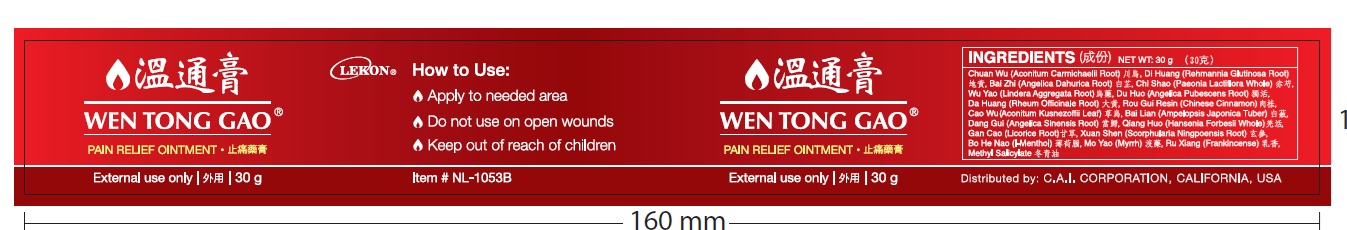 DRUG LABEL: Wen Tong Gao
NDC: 85954-003 | Form: OINTMENT
Manufacturer: CAI Industries Corp.
Category: otc | Type: HUMAN OTC DRUG LABEL
Date: 20250821

ACTIVE INGREDIENTS: LEVOMENTHOL 15 g/100 g
INACTIVE INGREDIENTS: ACONITUM CARMICHAELII ROOT; REHMANNIA GLUTINOSA ROOT; ANGELICA DAHURICA ROOT; PAEONIA LACTIFLORA WHOLE; LINDERA AGGREGATA ROOT; ANGELICA PUBESCENS ROOT; RHEUM OFFICINALE ROOT; CHINESE CINNAMON; ACONITUM KUSNEZOFFII LEAF; AMPELOPSIS JAPONICA TUBER; ANGELICA SINENSIS ROOT; HANSENIA FORBESII WHOLE; LICORICE; SCROPHULARIA NINGPOENSIS ROOT; MENTHOL, (+)-; MYRRH; METHYL SALICYLATE

Active Ingredients

Menthol 15%

Purpose

External analgesic

Uses

Temporarily relieves muscle and joint pains: backaches, arthritis, strains, bruises, sprains

Warnings

For external use only

When using this product

- avoid contact with the eyes or mucous membranes
- do not use on wounds or broken skin

Stop use and ask a doctor if

- conditions worsen
- excessive skin irritation develops
- nausea, vomiting, abdominal discomfort, diarrhea, or a skin rash occurs
- symptoms persists for more than 7 days

If pregnant or breast-feeding, ask a doctor before use.

Keep out of reach of children. If swallowed, get medical help or contact a Poison Control Center right away.

Directions

- Adults and children 12 years of age and older: Apply it and massage into affected areas.
- Children under 12 years of age: consult your physician

Other Information

- Keep unused plasters in the pouch
- Store in a cool dry place at room temperature.

Inactive ingredients

Chuan Wu (Aconitum Carmichaelli Root), Di Huang (Rehmannia Glutinosa Root), Bai Zhi (Angelica Dahurica Root), Chi Shao (Paeonia Lactiflora Whole), Wu Yao (Lindera Aggregata Root), Du Huo (Angelica Pubescens Root), Da Huang (Rheum Officinale Root), Rou Gui Resin (Chinese Cinnamon), Cao Wu (Aconitum Kusnezoffii Leaf), Bai Lian (Ampelopsis Japonica Tuber), Dang Gui (Angelica Sinensis Root), Qiang Huo (Hansenia Forbsii Whole), Gan Cao (Licorice Root), Xuan Shen (Scrophularia Ningpoensis Root), Mo Yao (Myrrh), Ru Xiang (Frankincense), Methyl Salicylate